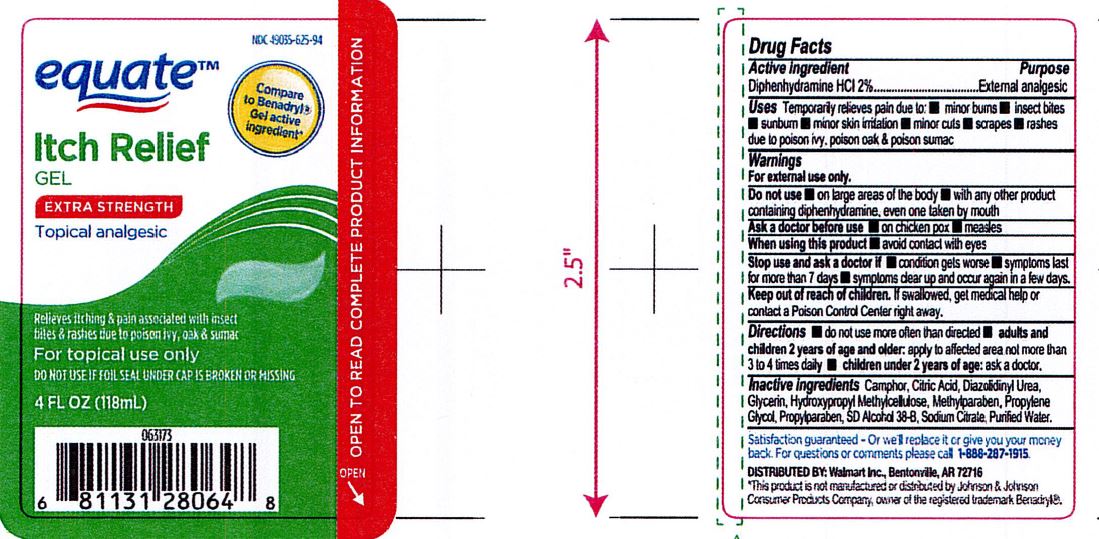 DRUG LABEL: Itch Relief Gel
NDC: 82645-901 | Form: GEL
Manufacturer: Pharma Nobis, LLC
Category: otc | Type: HUMAN OTC DRUG LABEL
Date: 20231222

ACTIVE INGREDIENTS: DIPHENHYDRAMINE HYDROCHLORIDE 2 mg/100 mL
INACTIVE INGREDIENTS: ANHYDROUS CITRIC ACID; CAMPHOR (SYNTHETIC); HYPROMELLOSE, UNSPECIFIED; ALCOHOL; METHYLPARABEN; PROPYLPARABEN; PROPYLENE GLYCOL; DIAZOLIDINYL UREA; SODIUM CITRATE; WATER; GLYCERIN

Private Label Itch Relief Gel

Do not use more often than directed.

Adults and children 2 years of age and older: apply to affected area not more than 3 to 4 times daily.

Children under 2 years of age: ask a doctor.

WARNINGS

For external use only.

INACTIVE INGREDIENT

Camphor, Citric Acid, Diazolidnyl Urea, Glycerin, Hydroxypropyl Methylcellulose, Methylparaben, Propylene Glycol, Propylparaben, SD Alcohol 38-B, Sodium Citrate, Purified Water.

INDICATIONS AND USAGE

Temporarily relieves pain due to: Minor burns, insect bites, sunburn, minor skin irritation, minor cuts, scrapes, rashes due to poison ivy, poison oak and poison sumac.

Keep out of reach of children. If swallowed, get medical help or contact a Poison Control Center right away.

PURPOSE

External Analgesic

ACTIVE INGREDIENT

Diphenhydramine HCl 2%

Equate Label

[